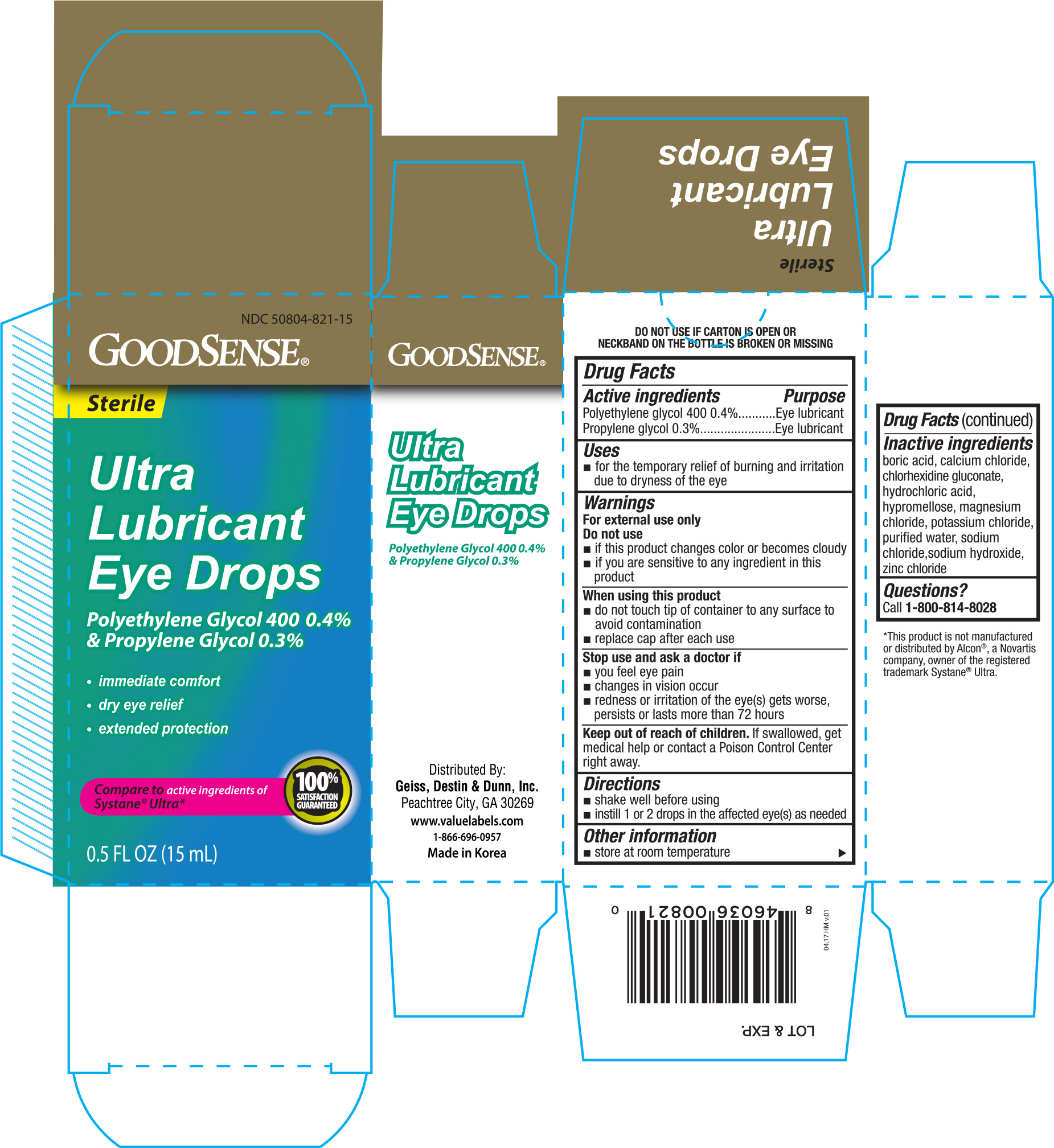 DRUG LABEL: Goodsense Ultra Lubricant
NDC: 50804-821 | Form: SOLUTION/ DROPS
Manufacturer: Geiss, Destin & Dunn, Inc
Category: otc | Type: HUMAN OTC DRUG LABEL
Date: 20170517

ACTIVE INGREDIENTS: POLYETHYLENE GLYCOL 400 4 mg/1 mL; PROPYLENE GLYCOL 3 mg/1 mL
INACTIVE INGREDIENTS: BORIC ACID; CALCIUM CHLORIDE; CHLORHEXIDINE GLUCONATE; HYDROCHLORIC ACID; HYPROMELLOSE, UNSPECIFIED; MAGNESIUM CHLORIDE; POTASSIUM CHLORIDE; WATER; SODIUM CHLORIDE; SODIUM HYDROXIDE; ZINC CHLORIDE

Active ingredients Purpose

Polyethlene glycol 400 0.4%.............Eye lubricant

Propylene glycol 0.3%.......................Eye lubricant

Uses

- for the temporary relief of burning and irritation due to dryness of the eye

Warnings

For external use only

Do not use

- if this product changes color or becomes cloudy
- if you are sensitive to any ingredient in this product

When using this product

- do not touch tip of container to any surface to avoid containation
- replace cap after each use

Stop use and ask a doctor if

- you feel eye pain
- changes in vision occur
- redness or irritation of the eye(s) gets worse, persists or lasts more than 72 hours

Keep out of reach of children. If swallowed, get medical help or contact a Poison Control Center right away.

Directions

- shake well before using
- instill 1 or 2 drops in the affected eye(s) as needed

Other information

- store at room temperature

Inactive ingredients

boric acid, calcium chloride, chlorhexidine gluconate, hydrochloric acid, hypromellose, magnesium chloride, potassium chloride, purified water, sodium chloride, sodium hydroxide, zinc chloride

DOSAGE AND ADMINISTRATION

Distributed By:

Geiss, Destin & Dunn, Inc.

Peachtree City, GA 30269

www.valuelabels.com

1-866-696-0957

Made in Korea